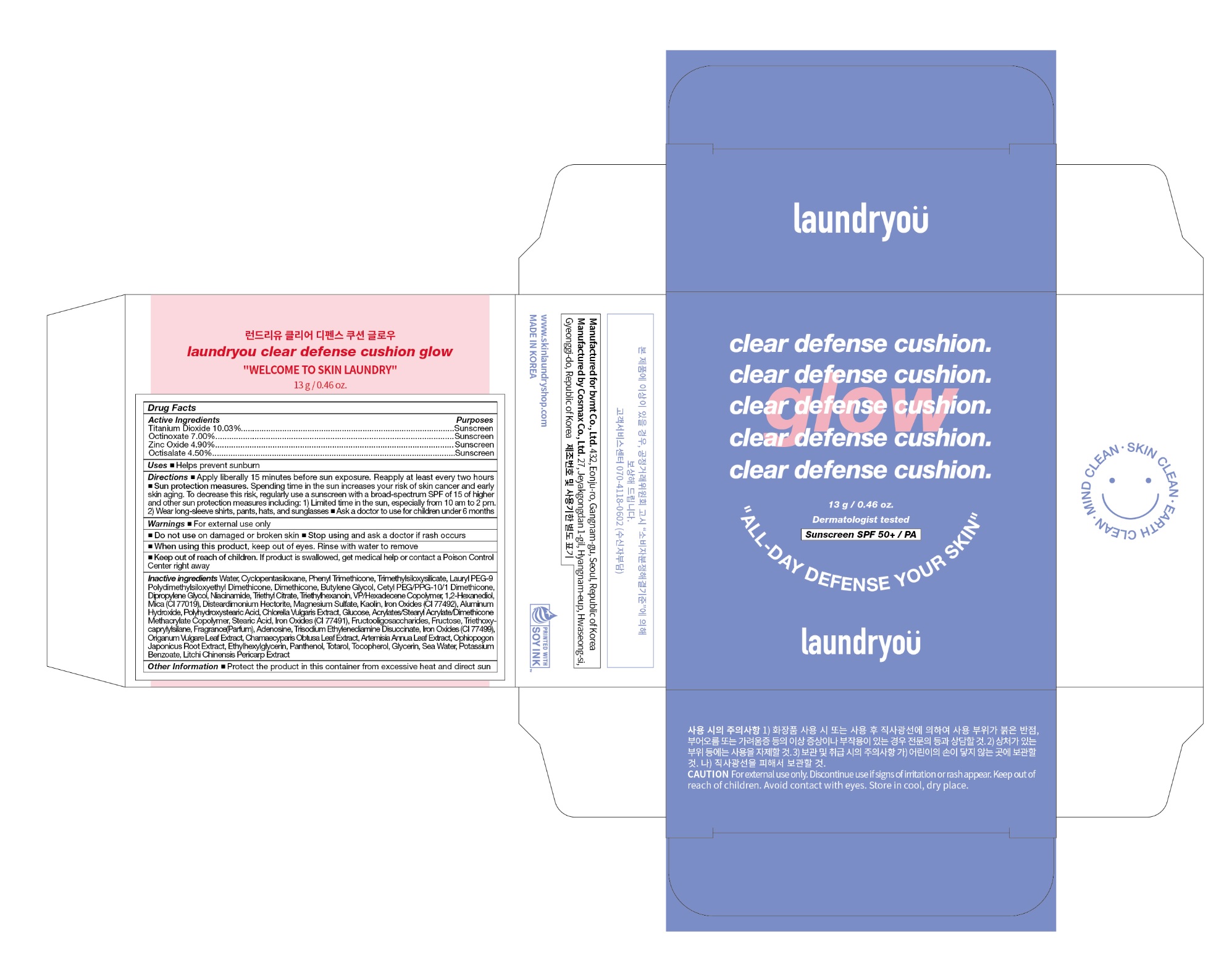 DRUG LABEL: LAUNDRYOU CLEAR DEFENSE CUSHION GLOW 21 UYUNI BEIGE
NDC: 83024-002 | Form: CREAM
Manufacturer: bvmt Co.,Ltd.
Category: otc | Type: HUMAN OTC DRUG LABEL
Date: 20221005

ACTIVE INGREDIENTS: TITANIUM DIOXIDE 10.03 g/100 g; OCTINOXATE 7 g/100 g; OCTISALATE 4.5 g/100 g; ZINC OXIDE 4.9 g/100 g
INACTIVE INGREDIENTS: WATER; CYCLOMETHICONE 5; PHENYL TRIMETHICONE; TRIMETHYLSILOXYSILICATE (M/Q 0.6-0.8); LAURYL PEG-9 POLYDIMETHYLSILOXYETHYL DIMETHICONE; DIMETHICONE; BUTYLENE GLYCOL; CETYL PEG/PPG-10/1 DIMETHICONE (HLB 4); DIPROPYLENE GLYCOL; NIACINAMIDE; TRIETHYL CITRATE; TRIETHYLHEXANOIN; VINYLPYRROLIDONE/HEXADECENE COPOLYMER; 1,2-HEXANEDIOL; MICA; DISTEARDIMONIUM HECTORITE; MAGNESIUM SULFATE, UNSPECIFIED FORM; KAOLIN; FERRIC OXIDE YELLOW; ALUMINUM HYDROXIDE; POLYHYDROXYSTEARIC ACID (2300 MW); CHLORELLA VULGARIS; ANHYDROUS DEXTROSE; STEARIC ACID; FERRIC OXIDE RED; FRUCTOSE; TRIETHOXYCAPRYLYLSILANE; ADENOSINE; TRISODIUM ETHYLENEDIAMINE DISUCCINATE; FERROSOFERRIC OXIDE; OREGANO; CHAMAECYPARIS OBTUSA LEAF; ARTEMISIA ANNUA LEAF; OPHIOPOGON JAPONICUS ROOT; ETHYLHEXYLGLYCERIN; PANTHENOL; TOTAROL; TOCOPHEROL; GLYCERIN; SODIUM CHLORIDE; POTASSIUM BENZOATE; LITCHI FRUIT

83024-002_LAUNDRYOU CLEAR DEFENSE CUSHION GLOW 21 UYUNI BEIGE

ACTIVE INGREDIENT

Titanium Dioxide 10.03%
Octinoxate 7.00%

Zinc Oxide 4.90%

Octisalate 4.50%

PURPOSE

Sunscreen

DOSAGE AND ADMINISTRATION

- Apply liberally 15 minutes before sun exposure. Reapply at least every two hours
- Sun protection measures. Spending time in the sun increases your risk of skin cancer and early skin aging. To decrease this risk, regularly use a sunscreen with a broad-spectrum SPF of 15 of higher and other sun protection measures including: 1) Limited time in the sun, especially from 10 am to 2 pm. 2) Wear long-sleeve shirts, pants, hats, and sunglasses
- Ask a doctor to use for children under 6 months

INDICATIONS AND USAGE

Helps prevent sunburn

WARNINGS

For external use only

Do not use on damaged or broken skin

When using this product, keep out of eyes. Rinse with water to remove.

Stop using and ask a doctor if rash occurs.

KEEP OUT OF REACH OF CHILDREN

Keep out of reach of the children. If product is swallowed, get medical help or contact a poison control center right away.

INACTIVE INGREDIENT

Water, Cyclopentasiloxane, Phenyl Trimethicone, Trimethylsiloxysilicate, Lauryl PEG-9 Polydimethylsiloxyethyl Dimethicone, Dimethicone, Butylene Glycol, Cetyl PEG/PPG-10/1 Dimethicone, Dipropylene Glycol, Niacinamide, Triethyl Citrate, Triethylhexanoin, VP/Hexadecene Copolymer, 1,2-Hexanediol, Mica (CI 77019), Disteardimonium Hectorite, Magnesium Sulfate, Kaolin, Iron Oxides (CI 77492), Aluminum Hydroxide, Polyhydroxystearic Acid, Chlorella Vulgaris Extract, Glucose, Acrylates/Stearyl Acrylate/Dimethicone Methacrylate Copolymer, Stearic Acid, Iron Oxides (CI 77491), Fructooligosaccharides, Fructose, Triethoxycaprylylsilane, Fragrance(Parfum), Adenosine, Trisodium Ethylenediamine Disuccinate, Iron Oxides (CI 77499), Origanum Vulgare Leaf Extract, Chamaecyparis Obtusa Leaf Extract, Artemisia Annua Leaf Extract, Ophiopogon Japonicus Root Extract, Ethylhexylglycerin, Panthenol, Totarol, Tocopherol, Glycerin, Sea Water, Potassium Benzoate, Litchi Chinensis Pericarp Extract

OTHER SAFETY INFORMATION

Protect the product in the container from excessive heat and direct sun